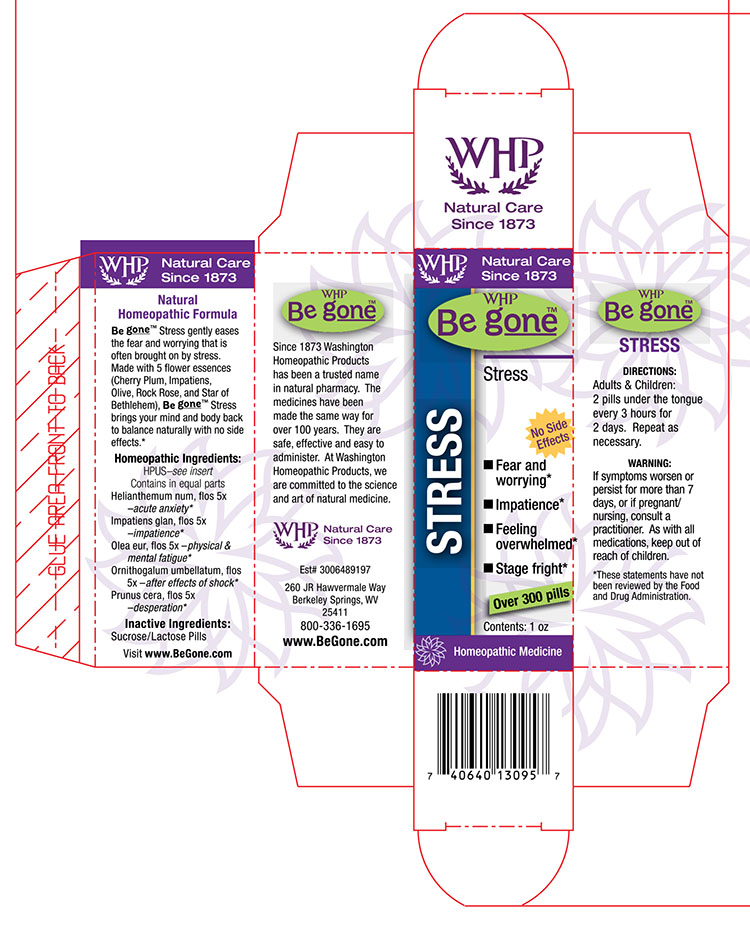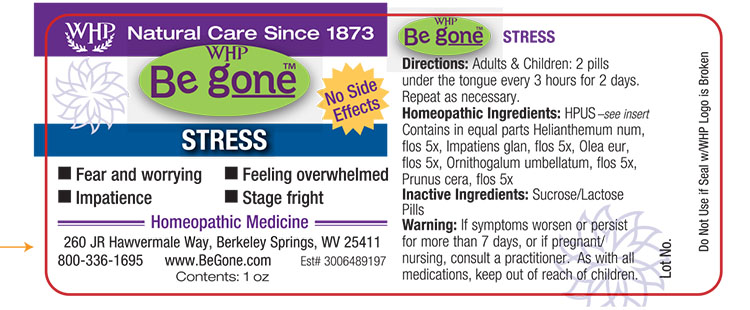 DRUG LABEL: WHP Be gone Stress
NDC: 68428-999 | Form: PELLET
Manufacturer: Washington Homeopathic Products
Category: homeopathic | Type: HUMAN OTC DRUG LABEL
Date: 20160513

ACTIVE INGREDIENTS: HELIANTHEMUM NUMMULARIUM FLOWER 5 [hp_X]/1 1; IMPATIENS GLANDULIFERA FLOWER 5 [hp_X]/1 1; OLEA EUROPAEA FLOWER 5 [hp_X]/1 1; ORNITHOGALUM UMBELLATUM FLOWERING TOP 5 [hp_X]/1 1; PRUNUS CERASIFERA FLOWER 5 [hp_X]/1 1
INACTIVE INGREDIENTS: SUCROSE; LACTOSE

DRUG FACTS

ACTIVE INGREDIENTS

HELIANTHEMUM NUM, FLOS

IMPATIENS GLAN, FLOS

OLEA EUR, FLOS

ORNITHOGALUM UMBELLATUM, FLOS

PRUNUS CERA, FLOS

USES

Temporarily relieves pain and other symptoms associated with insect bites and stings, including mosquito, ant, bee, and wasp.

KEEP OUT OF REACH OF CHILDREN

As wtih all medications, keep out of reach of children.

INDICATIONS

Helianthemum num, flos 5x (Rock Rose) –acute anxiety*

Impatiens glan, flos 5x (Impatiens) –impatience*

Olea eur, flos 5x (Olive) –mental fatigue*

Ornithogalum umbellatum, flos 5x (Star of Bethlehem) –after effects of shock*

Prunus cera, flos 5x (Cherry Plum) –desperation

■ Fear and worrying ■ Impatience ■ Feeling overwhelmed ■ Stage fright

*These statements have not been reviewed by the Food and Drug Administration.

STOP USE AND ASK DOCTOR

If symptoms persist or recur, discontinue use. If pregnant or nursing a baby, consult a licensed practitioner before using this product.

DIRECTIONS

Adults: 2 pills every 3 hours for 2 days. Then 2 pills morning and night for 2 weeks.

Children: 1 pill. Repeat as necessary.

INACTIVE INGREDIENTS

Sucrose/Lactose Pills